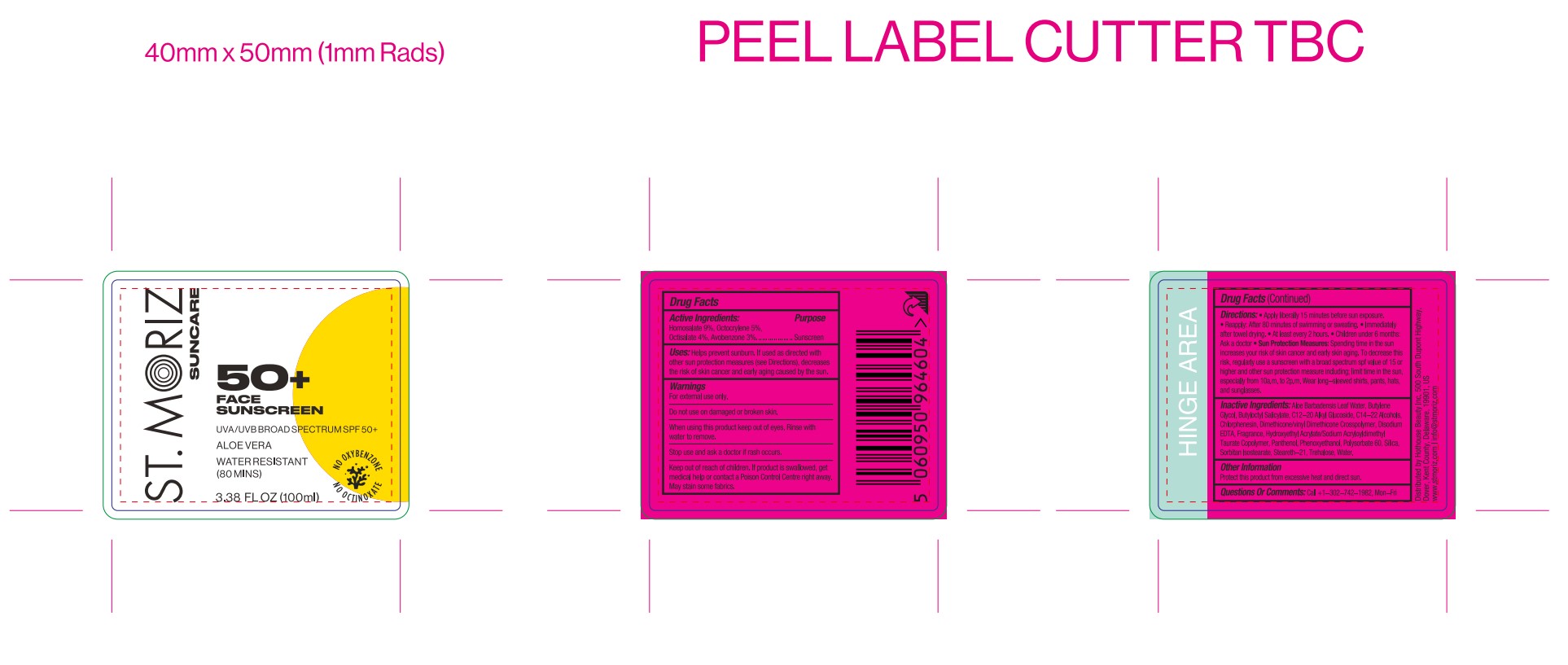 DRUG LABEL: St Moriz suncare face sunscreen spf50
NDC: 87283-007 | Form: LOTION
Manufacturer: Aopline Biotechnology (Guangzhou) Co., Ltd.
Category: otc | Type: HUMAN OTC DRUG LABEL
Date: 20260108

ACTIVE INGREDIENTS: HOMOSALATE 16.2 g/180 mL; AVOBENZONE 5.4 g/180 mL; OCTISALATE 7.2 g/180 mL; OCTOCRYLENE 9 g/180 mL
INACTIVE INGREDIENTS: C14-22 ALCOHOLS; BUTYLENE GLYCOL; CHLORPHENESIN; ALOE BARBADENSIS LEAF POWDER; DIMETHICONE/VINYL DIMETHICONE CROSSPOLYMER (SOFT PARTICLE); TREHALOSE; SILICA; STEARETH-21; SORBITAN ISOSTEARATE; PANTHENOL; C12-20 ALKYL GLUCOSIDE; EDETATE DISODIUM; WATER; POLYSORBATE 60; BUTYLOCTYL SALICYLATE; HYDROXYETHYL ACRYLATE/SODIUM ACRYLOYLDIMETHYL TAURATE COPOLYMER (45000 MPA.S AT 1%); PHENOXYETHANOL

ACTIVE INGREDIENT

OCTOCRYLENE
OCTISALATE
AVOBENZONE
HOMOSALATE

PURPOSE

Sunscreen

Keep out of reach of children . If product is swallowed , get medical help or contact a
Poison Control Center right away

WARNINGS

For external use only .
Do not use on broken or damaged skin .
Stop use and ask a doctor if rash occurs
When using this product keep out of eyes . Rinse with water to remove .
Keep out of reach of children . If product is swallowed , get medical help or contact a
Poison Control Center right away .

INDICATIONS AND USAGE

Directions : Apply liberally 15 minutes before sun or water exposure. Works best on
moisturized skin.
Reapply:
After 80 minutes of swimming or sweating.
Immediately after towel drying.
At least every 2 hours.
Children under 6 months: Ask a doctor..

INACTIVE INGREDIENT

BUTYLENE GLYCOL
WATER
C14-22 ALCOHOLS
C12-20 ALKYL GLUCOSIDE
BUTYLOCTYL SALICYLATE
STEARETH-21
HYDROXYETHYL ACRYLATE/SODIUM ACRYLOYLDIMETHYL TAURATE COPOLYMER
POLYSORBATE 60
SORBITAN ISOSTEARATE
TREHALOSE
DIMETHICONE/VINYL DIMETHICONE CROSSPOLYMER
SILICA
PHENOXYETHANOL
CHLORPHENESIN
FRAGRANCE
DISODIUM EDTA
PANTHENOL
ALOE BARBADENSIS LEAF WATER